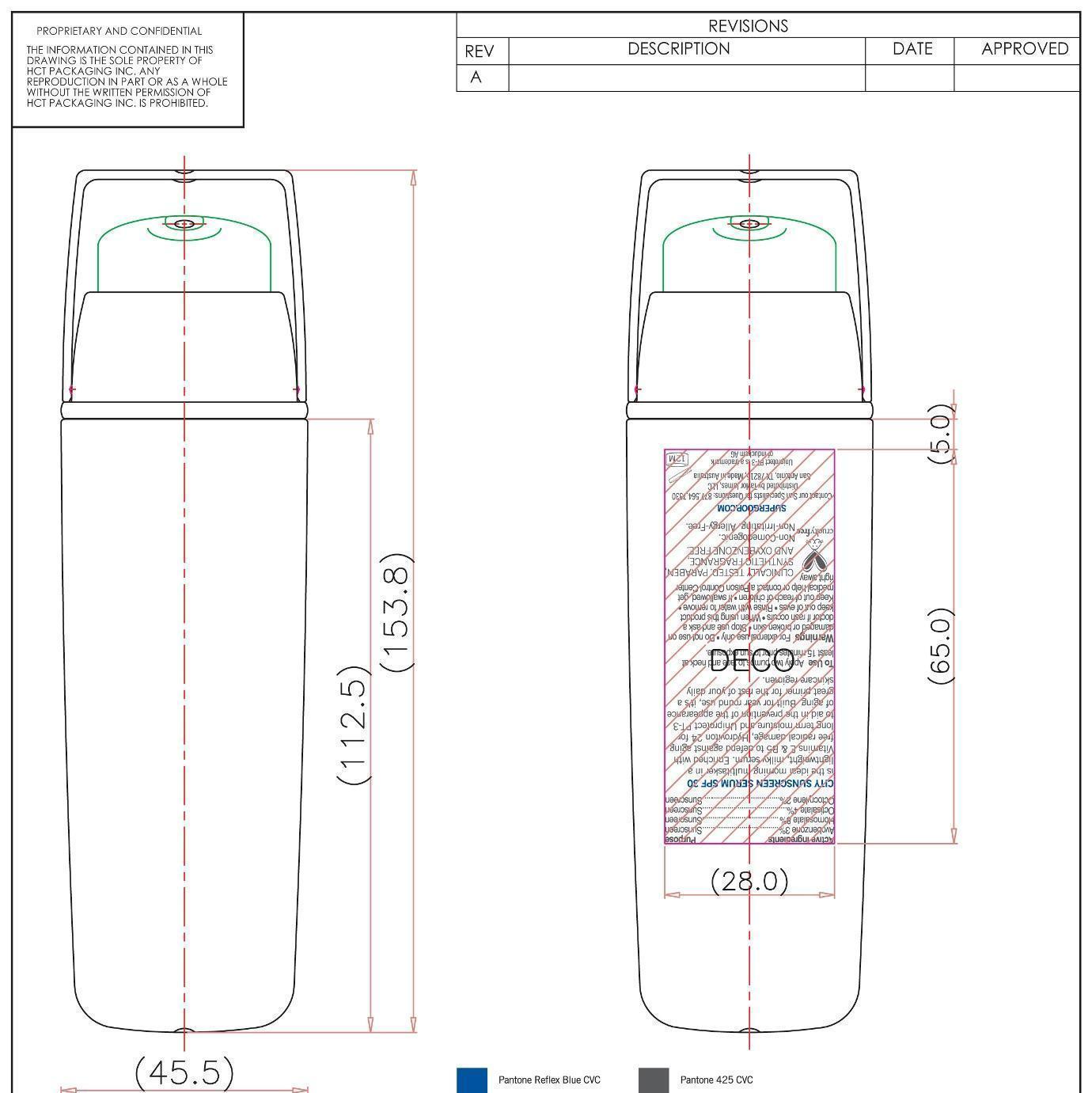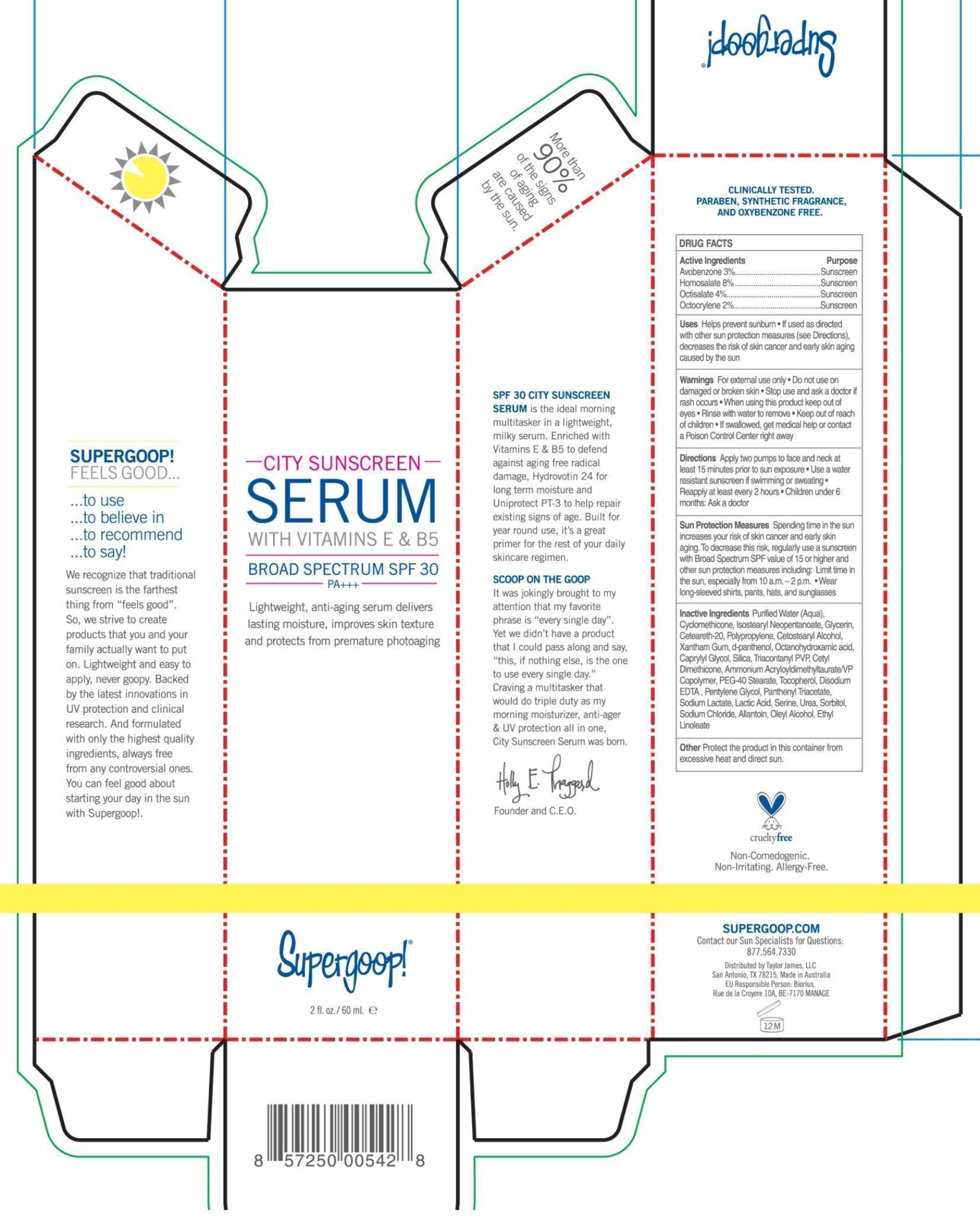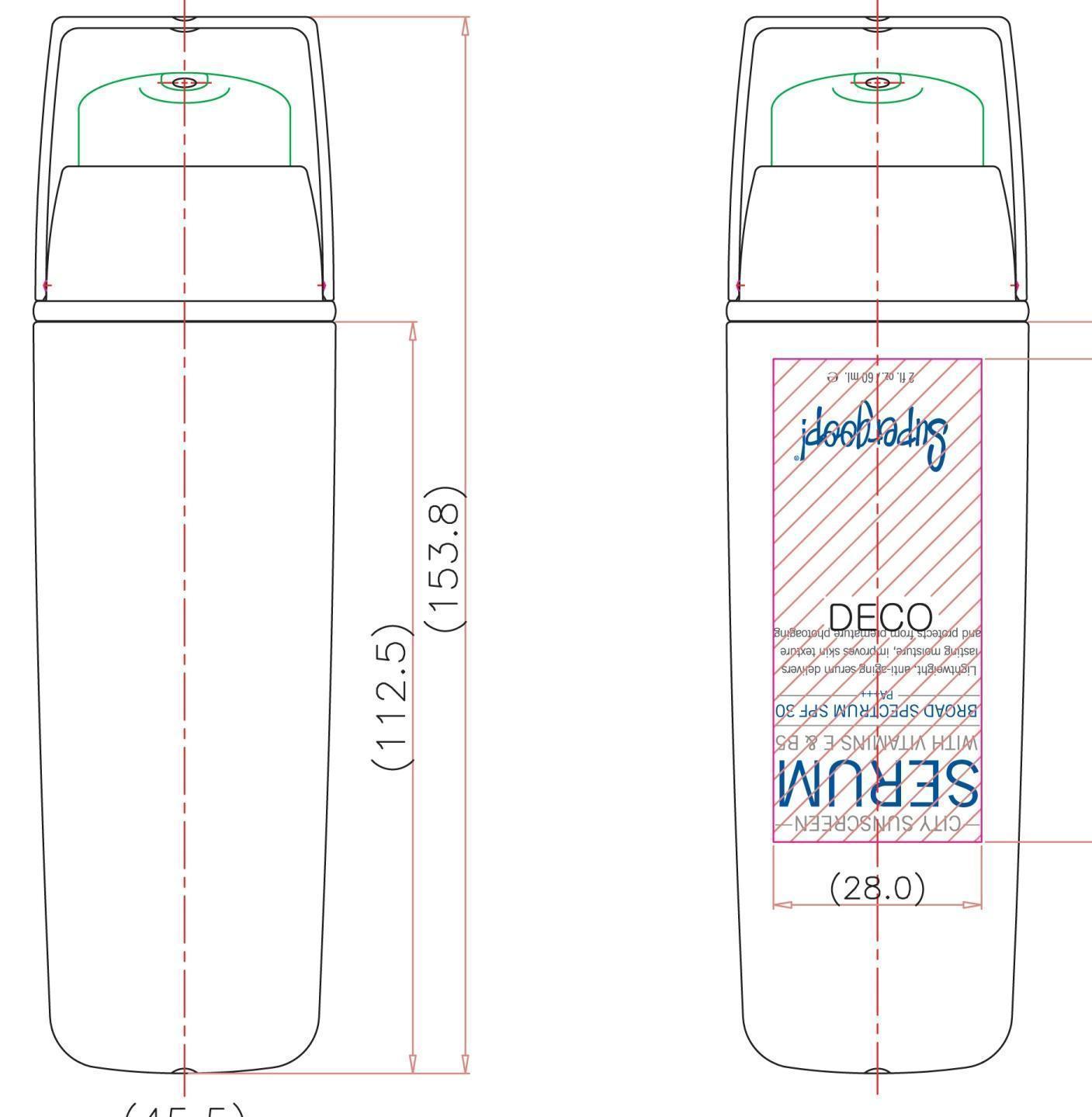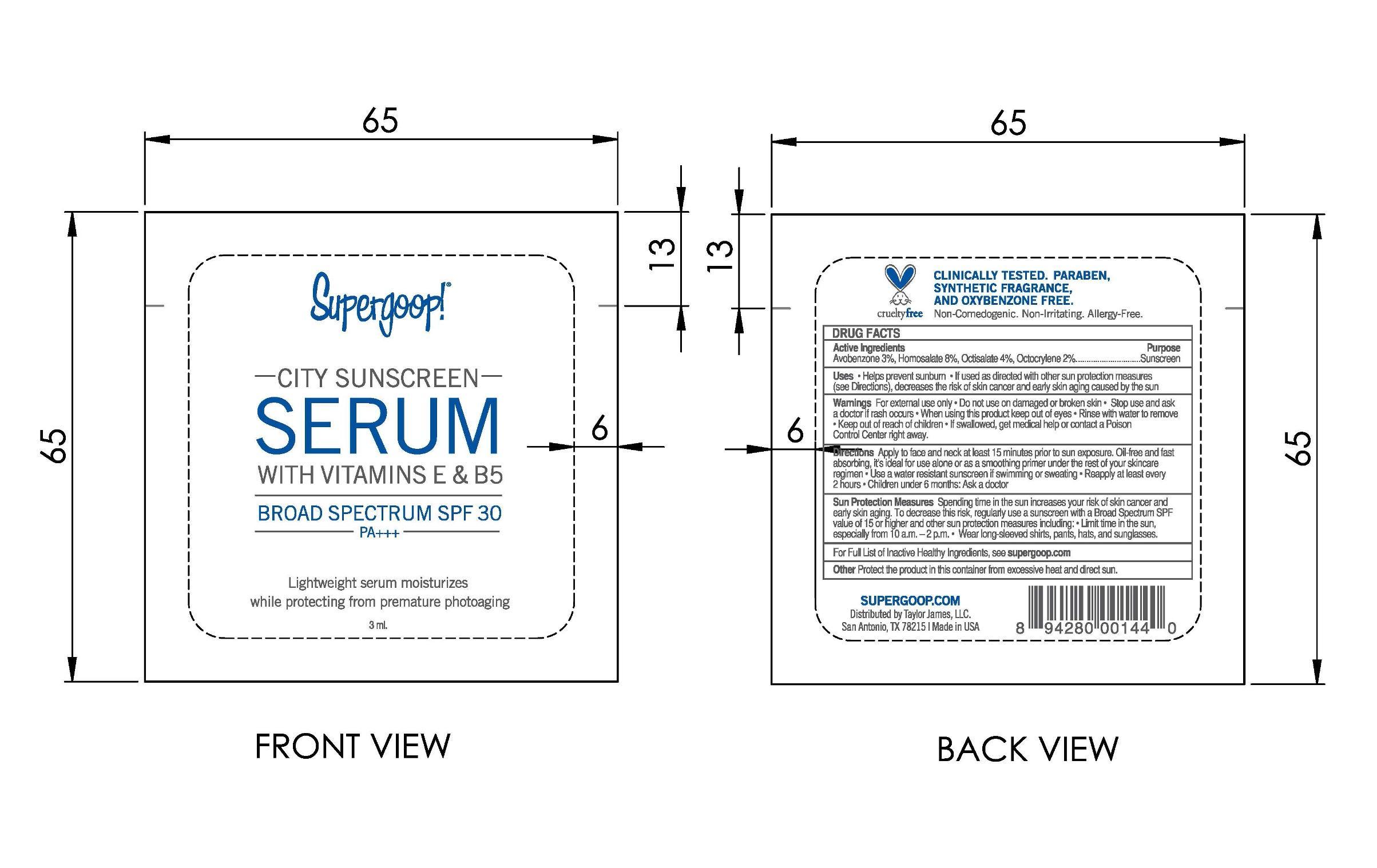 DRUG LABEL: City Sunscreen serum Broad Spectrum SPF 30
NDC: 70157-002 | Form: CREAM
Manufacturer: Baxter Laboratories Pty. Ltd.
Category: otc | Type: HUMAN OTC DRUG LABEL
Date: 20251022

ACTIVE INGREDIENTS: HOMOSALATE 8 g/100 mL; OCTISALATE 4 g/100 mL; AVOBENZONE 3 g/100 mL; OCTOCRYLENE 2 g/100 mL
INACTIVE INGREDIENTS: CYCLOMETHICONE; GLYCERIN; XANTHAN GUM; PANTHENOL; CAPRYLYL GLYCOL; SILICON DIOXIDE; POLYOXYL 40 STEARATE; EDETATE DISODIUM; PENTYLENE GLYCOL; SODIUM LACTATE; LACTIC ACID; SERINE; UREA; SORBITOL; SODIUM CHLORIDE; ALLANTOIN; OLEYL ALCOHOL; ETHYL LINOLEATE

City Sunscreen Serum Broad Spectrum SPF 30

Active ingredients: Purpose

Homosalate 8%, Octisalate 4%, Avobenzene 3%, Octocrylene 2% Sunscreen

Purpose

Uses Simultaneously protects skin, combats premature aging and moisturizes on contact

helps prevent sunburn

If used as directed with other sun protection measures (see directions), decreases the risk of skin cancer and early skin aging skin aging caused by the sun

Keep out of reach of children

Warnings

For external use only.

Do not use on damaged or broken skin

When using this product, keep out of of eyes.

Rinse with water to remove.

If swallowed, get medical help or contact a Poison Control Center right away.

DOSAGE AND ADMINISTRATION

Directions: Apply liberally 15 minutes before sun exposure

Use a water resistant sunscreen if swimming or sweating

Reapply at least every 2 hours

children under 6 months: ask a doctor

Sun Protection Measures: Spending time in the sun increases your risk of skin cancer and early skin aging. To decrease this risk, regularly use a sunscreenwith Broad Spectrum SPF value of 15 or higher and other sun protection measures including:

Limit time in the sun,especially from 10 a.m. -2p.m.

Wear long-sleeved shirts, pants, hats, and sunglasses

INACTIVE INGREDIENT

Inactive Ingredients Purified water (Aqua), Cyclometicone, Isostearyl Neopentanoate, Glycerin, Ceteareth-20, Polypropylene, Cetearyl Alcohol, Xanthan Gum, d-Panthenol, Octanohydroxamic acid, Caprylyl Glycol, Silica, Triacontanyl PVP, Cetyl Dimethicone, Ammonium Acryloyldimethyltaurate/VP Copolymer, PEG-40 Stearate, Tocopheryl, Disodium EDTA, Pentylene Glycol, Pantheyl Triacetate, Sodium Lactate, Lactic Acid, Serine, Urea, Sorbitol, Sodium Chloride, Allantoin, Oleyl Alcohol, Ethyl Linoleate.

PACKAGE LABEL

City Sunscreen

SERUM

With Vitamins E & B5

Supergoop!